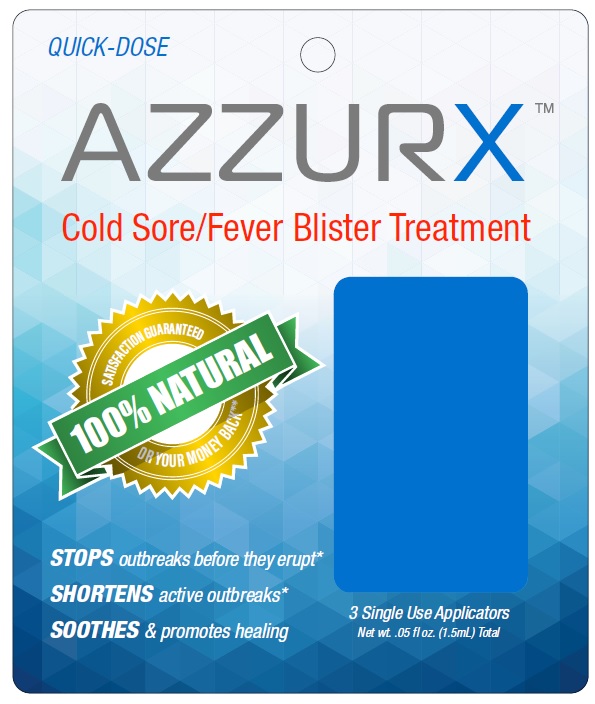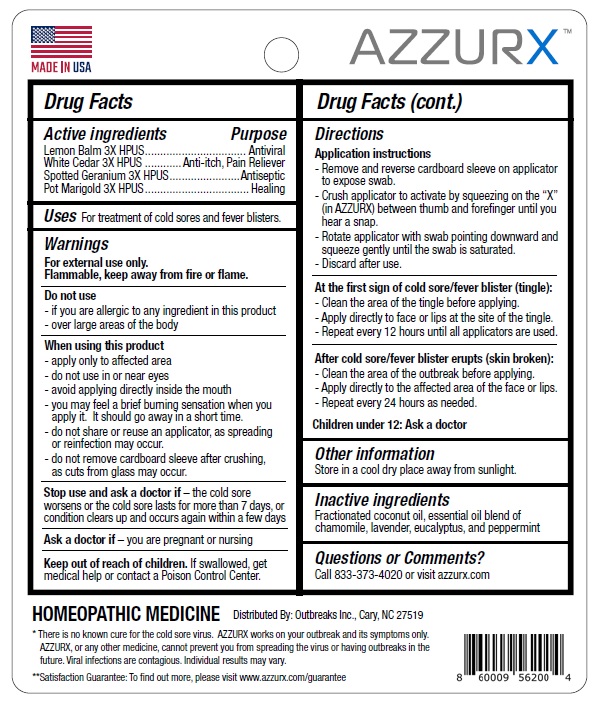 DRUG LABEL: AZZURX
NDC: 83243-001 | Form: LIQUID
Manufacturer: Outbreaks, Inc.
Category: homeopathic | Type: HUMAN OTC DRUG LABEL
Date: 20250114

ACTIVE INGREDIENTS: MELISSA OFFICINALIS LEAF 3 [hp_X]/0.5 mL; THUJA OCCIDENTALIS LEAF 3 [hp_X]/0.5 mL; GERANIUM MACULATUM ROOT 3 [hp_X]/0.5 mL; CALENDULA OFFICINALIS FLOWER 3 [hp_X]/0.5 mL
INACTIVE INGREDIENTS: MEDIUM-CHAIN TRIGLYCERIDES; CHAMOMILE FLOWER OIL; LAVENDER OIL; EUCALYPTUS OIL; PEPPERMINT OIL

Drug Facts

Active ingredients Purpose

Lemon Balm 3X HPUS Antiviral

White Cedar 3X HPUS Anti-itch, Pain Reliever

Spotted Geranium 3X HPUS Antiseptic

Pot Marigold 3X HPUS Healing

Uses

For treatment of cold sores and fever blisters.

Warnings

For external use only.
Flammable, keep away from fire or flame.

Do not use

- if you are allergic to any ingredient in this product
- over large areas of the body

When using this product

- apply only to affected area
- do not use in or near eyes
- avoid applying directly inside the mouth
- you may feel a brief burning sensation when you apply it. It should go away in a short time.
- do not share or reuse an applicator, as spreading or reinfection may occur.
- do not remove cardboard sleeve after crushing,as cuts from glass may occur.

Stop use and ask a doctor if – the cold sore worsens or the cold sore lasts for more than 7 days,

or condition clears up and occurs again within a few days

Ask a doctor if – you are pregnant or nursing

Keep out of reach of children. If swallowed, get medical help or contact a Poison Control Center.

Directions

Application instructions

- Remove and reverse cardboard sleeve on applicator to expose swab.
- Crush applicator to activate by squeezing on the “X” (in AZZURX) between thumb and forefinger until you hear a snap.
- Rotate applicator with swab pointing downward and squeeze gently until the swab is saturated.
- Discard after use.

At the first sign of cold sore/fever blister (tingle):

- Clean the area of the tingle before applying.
- Apply directly to face or lips at the site of the tingle.
- Repeat every 12 hours until all applicators are used.

After cold sore/fever blister erupts (skin broken):

- Clean the area of the outbreak before applying.
- Apply directly to the affected area of the face or lips.
- Repeat every 24 hours as needed

Children under 12: Ask a doctor

Other information

Store in a cool dry place away from sunlight.

Inactive ingredients

Fractionated coconut oil, essential oil blend of chamomile, lavender, eucalyptus, and peppermint

Questions or Comments?

Call 833-373-4020 or visit azzurx.com